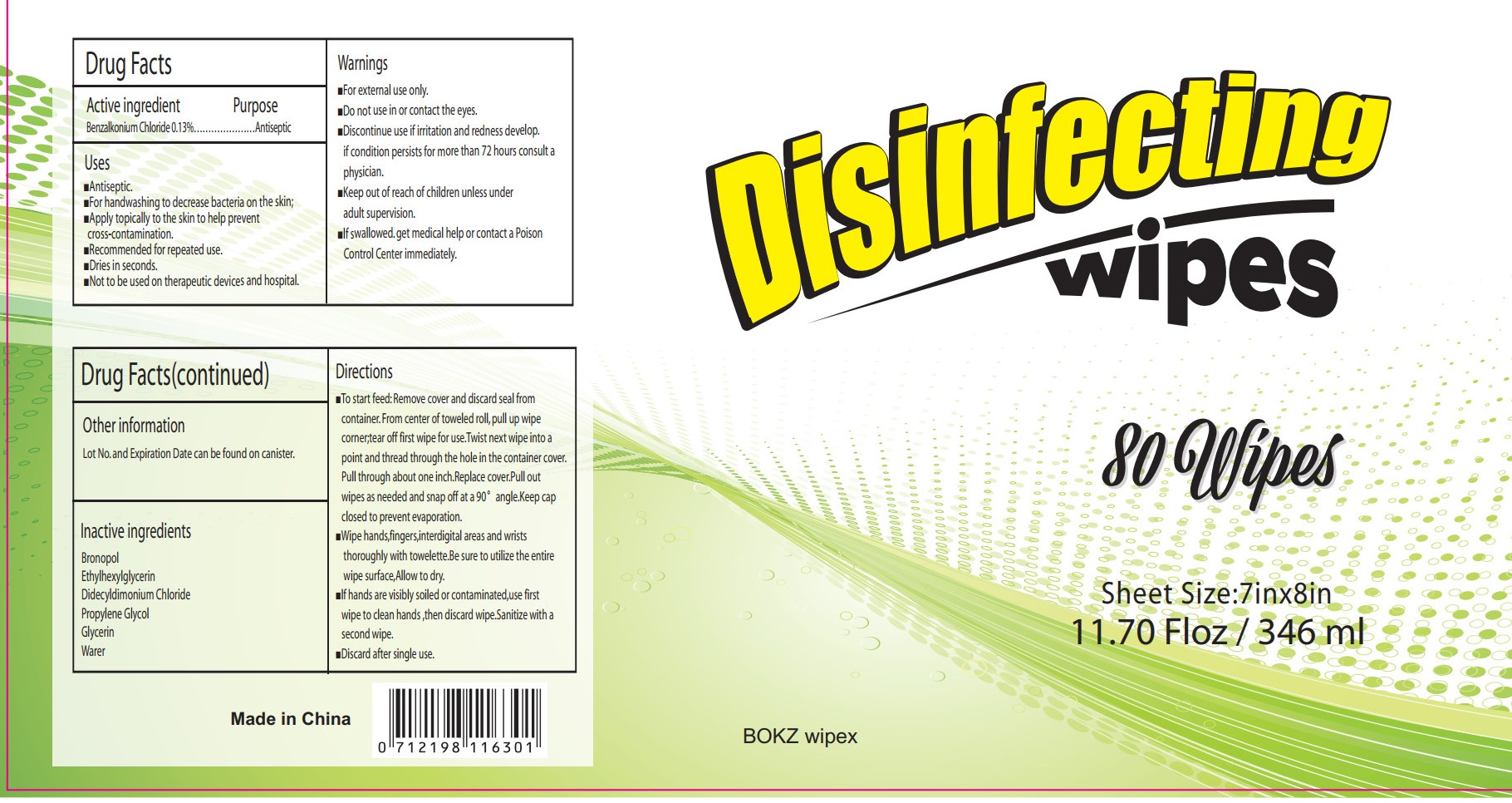 DRUG LABEL: Disinfecting Wipes
NDC: 76991-008 | Form: CLOTH
Manufacturer: Hefei Wenqi Industrial & Trade Co., Ltd
Category: otc | Type: HUMAN OTC DRUG LABEL
Date: 20200624

ACTIVE INGREDIENTS: BENZALKONIUM CHLORIDE 0.13 g/100 mL
INACTIVE INGREDIENTS: ETHYLHEXYLGLYCERIN; DIDECYLDIMONIUM CHLORIDE; GLYCERIN; PROPYLENE GLYCOL; WATER; STEPRONIN

Disinfecting Wipes

Active Ingredient(s)

Benzalkonium chloride 0.13%

Purpose

Antiseptic

Use

Antiseptic.
For handwashing to decrease bacteria on the skin
Apply topically to the skin to help prevent cross-contamination
Recommended for repeated use.
Dries in seconds
Not to be used on therapeutic devices and hospital.

Warnings

For extemal use only
Do not use in or contact the eyes
Discontinue useif irritation and redness develop. if condition persists for more than 72 hours consult a physician.
keep out of reach of children unless under adult supervision.
lf swallowed. get medical help or contact a Poison Control Center immediately.

Do not use in or contact the eyes
Discontinue useif irritation and redness develop. if condition persists for more than 72 hours consult a physician.

WHEN USING

Pull through about one inch. Replace cover Pull out wipes as needed and snap off at a 90° angle. Keep cap closed to prevent evaporation
Wipe hands, fingers, interdigital areas and wrists thoroughly with towelette. Be sure to utilize the entire wipe surface, Allow to dry
lf hands are visibly soiled or contaminated use first wipe to clean hands then discard wipe Sanitize with a second wipe discard after single use.

STOP USE

/

keep out of reach of children unless under adult supervision.
lf swallowed. get medical help or contact a Poison Control Center immediately.

Directions

To start feed: Remove cover and discard seal from container. From center of toweled roll, pull up wipe corner, tear off first wipe for use. Twist next wipe into a point and thread through the hole in the container cover.

Other information

Lot No. and Expiration Date can be found on canister.

Inactive ingredients

Bronco
Ethylhexylglycerin
Didecyldimonium Chloride
Propylene Glycol
Glycerin
water